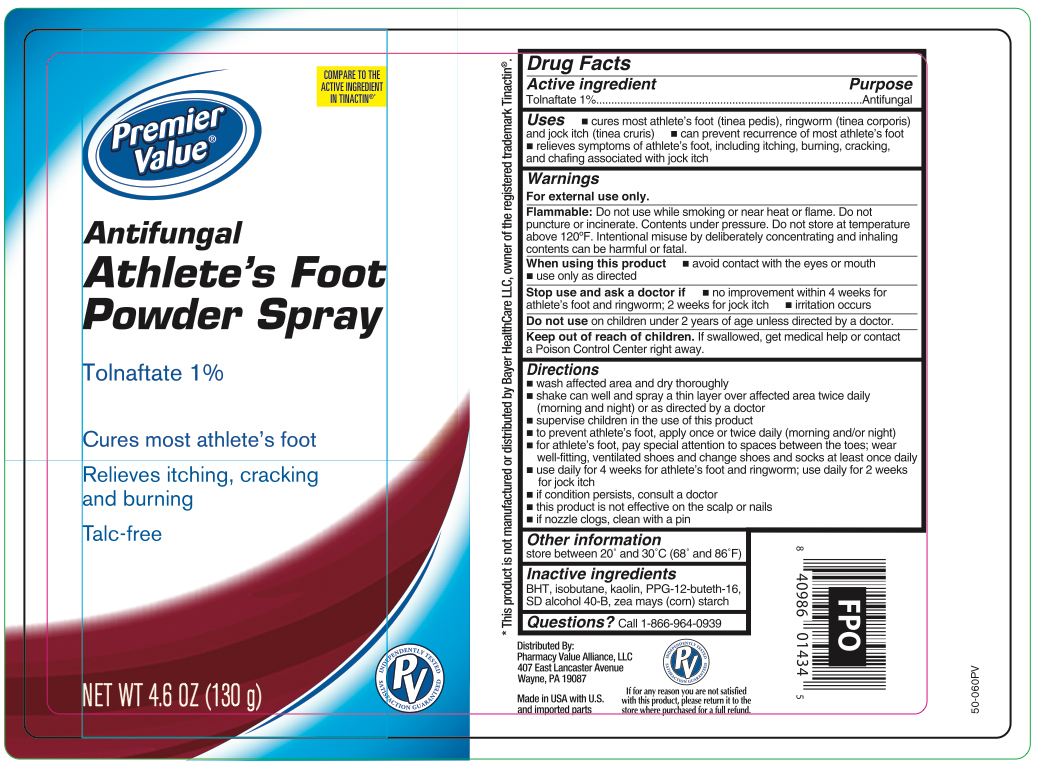 DRUG LABEL: Tolnafate
NDC: 68016-663 | Form: AEROSOL, SPRAY
Manufacturer: Chain Drug Consortium, LLC
Category: otc | Type: HUMAN OTC DRUG LABEL
Date: 20260212

ACTIVE INGREDIENTS: TOLNAFTATE 1.3 g/130 g
INACTIVE INGREDIENTS: BUTYLATED HYDROXYTOLUENE; ISOBUTANE; KAOLIN; PPG-12-BUTETH-16; ALCOHOL; ZEA MAYS SUBSP. MAYS WHOLE

Premier Value Tolnaftate Powder Spray - Talc Free

Active ingredient

Tolnaftate 1%

Purpose

Antifungal

Uses

- cures most athlete's foot (tinea pedis) and ringworm (tinea corporis)
- if used daily, can prevent recurrence of athlete's foot
- relieves sypmtoms of athlete's foot, including itching, burning and cracking

WARNINGS

For external use only.

Flammable:

Do not use while smoking or near heat or flame. Do not puncture or incinerate. Contents under pressure. Do not store at temperature above 120ºF

When using this product

- do not get into eyes or mouth, if products get into eyes, rinse eyes thoroughly with water
- use only as directed

Intentional misuse by deliberately concentrating and inhaling contents cans be harmful or fatal.

Stop use and ask a doctor if

- irritation occurs
- no improvement within 4 weeks

Keep out of reach of children.

If swallowed, get medical help or contact a Poison Control Center right away. Do not use on children under 2 years of age unless directed by a doctor.

Directions

- wash affected area and dry thoroughly
- shake can well and spray a thin layer over affected area twice daily (morning and night)
- supervise children in the use of this product
- for athlete's foot: pay special attention to spaces between the toes, wear well-fitting, ventilated shoes and change shoes and socks at least once daily
- use daily for 4 weeks; if conditions persist, consult a doctorto prevent athlete's foot, apply once or twice daily (morning and/or night)in case of clogging, clear nozzle under running water

Other information

store between 20º and 30ºC (68ºF and 86º)

Inactive ingredients

BHT, Isobutane, Kaolin, PPG-12-Buteth-16, SD Alcohol 40-B, Zea Mays (Corn) Starch

Questions?

call 1-866-964-0939

Principal Display Panel

Premier Value

Antifungal

Athlete's Foot Powder Spray

Tolnaftate 1%

Cures most athlete's foot

Relieves itching & burning

Talc Free

NET WT 4.6 OZ (130g)